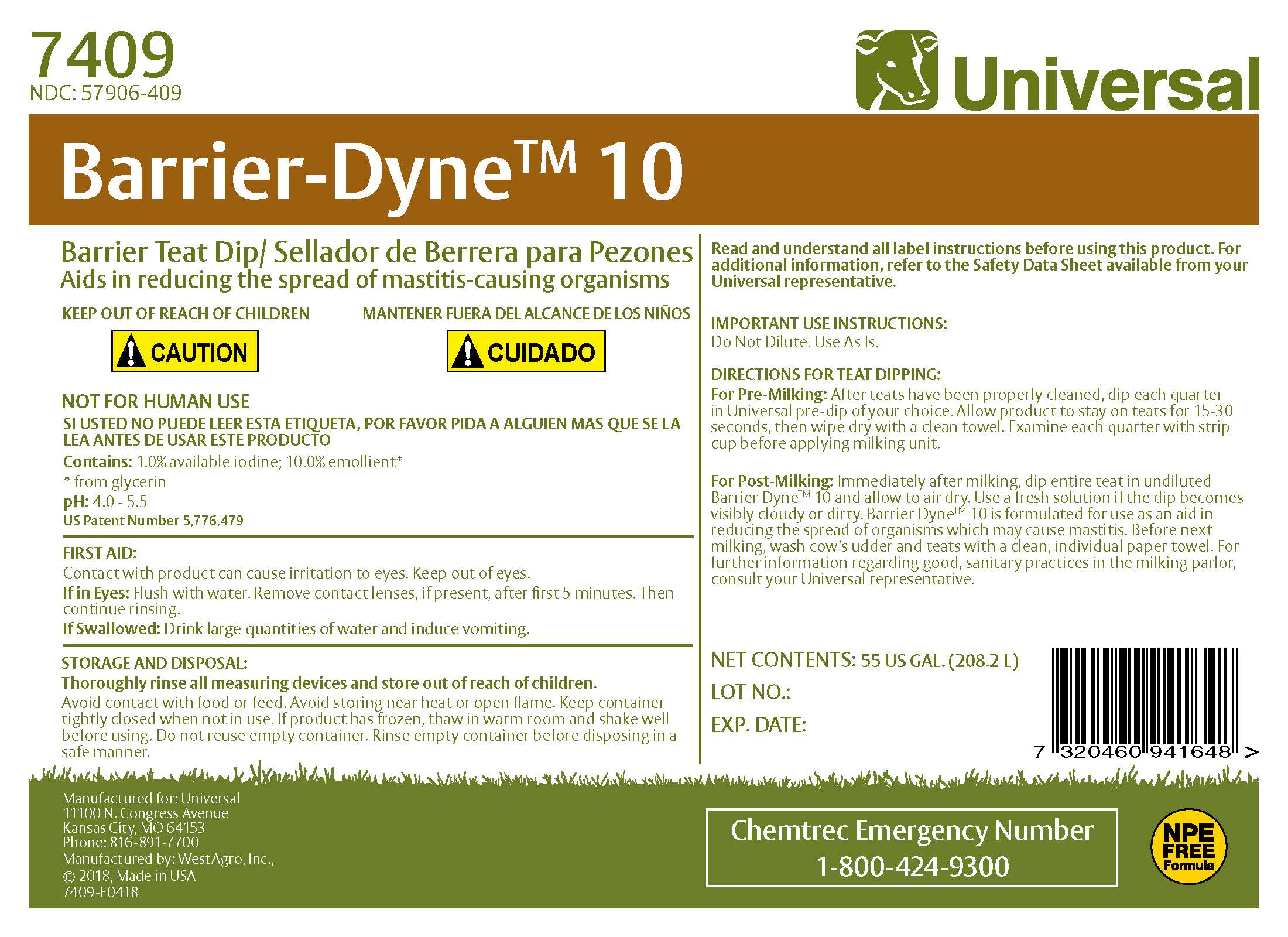 DRUG LABEL: Barrier-Dyne 10
NDC: 57906-409 | Form: SOLUTION
Manufacturer: Universal
Category: animal | Type: OTC ANIMAL DRUG LABEL
Date: 20220120

ACTIVE INGREDIENTS: IODINE 10.3 g/1 L

Universal Barrier-Dyne 10 Barrier Teat Dip / Sellador de Barrera para Pezones

INDICATIONS AND USAGE

Important Use Instructions
DO NOT DILUTE. USE AS IS.
Read and understand all label instructions before using this product. For additional information, refer to the Material Safety Data Sheet available from your Universal representative.
DIRECTIONS FOR TEAT DIPPING
FOR PRE-MILKING:
After teats have been properly cleaned, dip each quarter in Universal pre-dip of your choice. Allow product to stay on teats 15-30 seconds, then wipe dry with a clean towel. Examine each quarter with strip cup before applying milking unit.
FOR POST-MILKING:
Immediately after milking, dip entire teat in undiluted Barrier-Dyne 10 and allow to air dry. Use a fresh solution if the dip becomes visibly cloudy or dirty. Barrier-Dyne 10 is formulated for use as an aid in reducing the spread of organisms which may cause mastitis. Before next milking, wash cow's udder and teats with clean individual paper towel. For further information regarding good sanitary practice in the milking parlor, consult your Universal representative.

FIRST AID
Contact with product can cause irritation to eyes. Keep out of eyes.
Eye Contact: Flush with water. Remove contact lenses after first 5 minutes, if present, then continue flushing.
If Swallowed: Drink large quantities of water and induce vomiting.

STORAGE AND DISPOSAL
THOROUGHLY RINSE ALL MEASURING DEVICES AND STORE OUT OF REACH OF CHILDREN. Avoid contact with food or feed. Avoid storing near heat or open flame. Keep container tightly closed when not in use. If product has frozen, thaw in warm room and shake well before using. Do not reuse empty container. Rinse container before disposing in a safe manner.

KEEP OUT OF REACH OF CHILDREN
MANTENER FUERA DEL ALCANCE DE LOS NINOS

! CAUTION ! CUIDADO

SI USTED NO PUEDE LEER ESTA ETIQUETA, POR FAVOR PIDA A ALGUIEN MAS QUE SE LA LEA ANTES DE USAR ESTE PRODUCTO

ACTIVE INGREDIENT

Contains: 1% available iodine
10% glycerin

pH: 4.0-5.5

US Patent Number 5,776,479

Manufactured for: Universal
11100 N. Congress Avenue
Kansas City, MO 64153
Phone: 816-891-7700
Manufactured by: WestAgro, Inc.
©2018, Made in USA

Chemtrec Emergency Number
1-800-424-9300

Net Contents:

Lot No.:

Exp. Date: